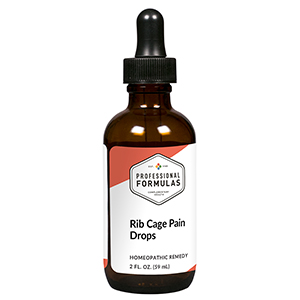 DRUG LABEL: Rib Cage Pain Drops
NDC: 63083-2056 | Form: LIQUID
Manufacturer: Professional Complementary Health Formulas
Category: homeopathic | Type: HUMAN OTC DRUG LABEL
Date: 20190815

ACTIVE INGREDIENTS: APIS MELLIFERA 6 [hp_X]/59 mL; SILVER NITRATE 6 [hp_X]/59 mL; ANHYDROUS DIBASIC CALCIUM PHOSPHATE 6 [hp_X]/59 mL; RUTA GRAVEOLENS FLOWERING TOP 6 [hp_X]/59 mL; ARSENIC TRIOXIDE 12 [hp_X]/59 mL; BOS TAURUS CARTILAGE 12 [hp_X]/59 mL; DELPHINIUM STAPHISAGRIA SEED 12 [hp_X]/59 mL; BOS TAURUS BONE MARROW 12 [hp_X]/59 mL; TOXICODENDRON PUBESCENS LEAF 30 [hp_X]/59 mL
INACTIVE INGREDIENTS: ALCOHOL; WATER

C56

ACTIVE INGREDIENTS

Apis mellifica 6X
Argentum nitricum 6X
Calcarea phosphorica 6X
Ruta graveolens 6X, 12X
Arsenicum album 12X
Intercostal cartilage 12X
Staphysagria 12X
Rib 12X, 30X
Rhus toxicodendron 30X

QUESTIONS

Professional Formulas

PO Box 2034 Lake Oswego, OR 97035

INDICATIONS

For the temporary relief of pain or tenderness of the chest or back in the area of the ribs.*

PURPOSE

*Claims based on traditional homeopathic practice, not accepted medical evidence. Not FDA evaluated.

WARNINGS

Severe or persistent symptoms may be a sign of a serious condition. Consult a doctor promptly if you are experiencing unexplained severe pain in your rib cage, chest pain, difficulty breathing, or severe shortness of breath. Keep out of the reach of children. In case of overdose, get medical help or contact a poison control center right away. If pregnant or breastfeeding, ask a healthcare professional before use.

Keep out of the reach of children.

PREGNANCY OR BREAST FEEDING

If pregnant or breastfeeding, ask a healthcare professional before use.

DIRECTIONS

Place drops under tongue 30 minutes before/after meals. Adults and children 12 years and over: Take 10 drops up to 3 times per day for up to 6 weeks. For immediate onset of symptoms, take 10 to 15 drops every 15 minutes up to 3 hours. For less severe symptoms, take 10-15 drops hourly up to 8 hours. Consult a physician for use in children under 12 years of age.

OTHER INFORMATION

Tamper resistant. If seal is broken, do not use. After opening, close container tightly and store at room temperature away from heat.

INACTIVE INGREDIENTS

20% ethanol, purified water.

LABEL

Est 1985

Professional Formulas

Complementary Health

Rib Cage Pain Drops

Homeopathic Remedy

2 FL. OZ. (59 mL)